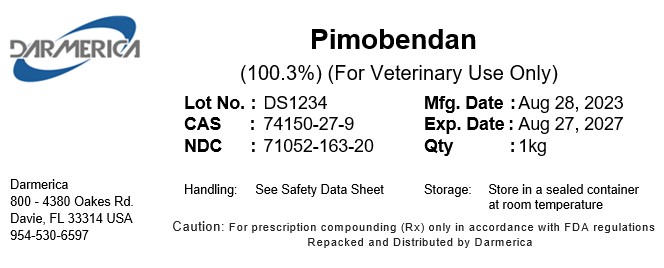 DRUG LABEL: Pimobendan
NDC: 71052-163 | Form: POWDER
Manufacturer: DARMERICA, LLC
Category: other | Type: BULK INGREDIENT - ANIMAL DRUG
Date: 20250827

ACTIVE INGREDIENTS: Pimobendan 1 kg/1 kg

Pimobendan